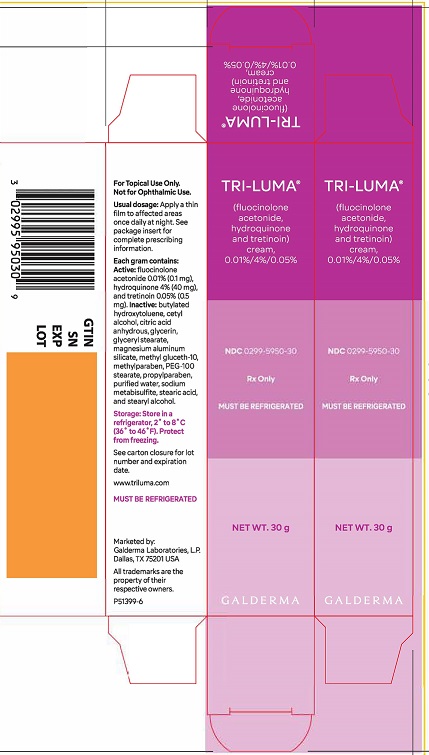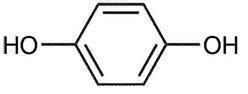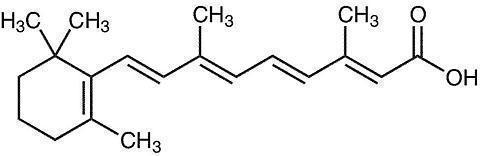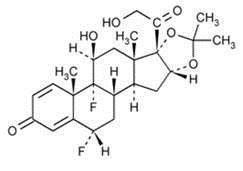 DRUG LABEL: TRI-LUMA
NDC: 0299-5950 | Form: CREAM
Manufacturer: Galderma Laboratories, L.P.
Category: prescription | Type: HUMAN PRESCRIPTION DRUG LABEL
Date: 20241024

ACTIVE INGREDIENTS: FLUOCINOLONE ACETONIDE 0.1 mg/1 g; HYDROQUINONE 40 mg/1 g; TRETINOIN 0.5 mg/1 g
INACTIVE INGREDIENTS: BUTYLATED HYDROXYTOLUENE; CETYL ALCOHOL; ANHYDROUS CITRIC ACID; GLYCERIN; GLYCERYL MONOSTEARATE; MAGNESIUM ALUMINUM SILICATE; METHYL GLUCETH-10; METHYLPARABEN; PEG-100 STEARATE; PROPYLPARABEN; WATER; SODIUM METABISULFITE; STEARIC ACID; STEARYL ALCOHOL

HIGHLIGHTS OF PRESCRIBING INFORMATION

These highlights do not include all the information needed to use TRI-LUMA Cream safely and effectively. See full prescribing information for TRI-LUMA Cream.
TRI-LUMA®(fluocinolone acetonide, hydroquinone, tretinoin) cream, 0.01%/4%/0.05% for topical use
Initial U.S. Approval: 2002

1 INDICATIONS AND USAGE

TRI-LUMA Cream is a combination of fluocinolone acetonide (a corticosteroid), hydroquinone (a melanin synthesis inhibitor), and tretinoin (a retinoid) that is indicated for the short-term treatment of moderate to severe melasma of the face, in the presence of measures for sun avoidance, including the use of sunscreens. (1)

2 DOSAGE AND ADMINISTRATION

- Apply a thin film to the affected area once daily, at least 30 minutes before bedtime. (2)
- During the day, use a sunscreen of SPF 30, and wear protective clothing. Avoid sunlight exposure. (2)

3 DOSAGE FORMS AND STRENGTHS

- Cream, 0.01%/4%/0.05%. Each gram of TRI-LUMA Cream contains 0.1 mg of fluocinolone acetonide, 40 mg of hydroquinone, and 0.5 mg of tretinoin. (3)

4 CONTRAINDICATIONS

- TRI-LUMA Cream is contraindicated in individuals with a history of hypersensitivity to this product or any of its components. (4)

5 WARNINGS AND PRECAUTIONS

- TRI-LUMA Cream contains sodium metabisulfite, a sulfite that may cause allergic-type reactions including anaphylactic symptoms and life-threatening asthmatic episodes in susceptible people. If anaphylaxis, asthma or other clinically significant hypersensitivity reaction occurs, institute appropriate therapy and discontinue TRI-LUMA. (5.1)
- TRI-LUMA Cream contains hydroquinone, which may produce exogenous ochronosis, a gradual blue-black darkening of the skin, the occurrence of which should prompt discontinuation of therapy. (5.2)

6 ADVERSE REACTIONS

Most common adverse reactions (incidence > 5%) are erythema, desquamation, burning, dryness, pruritus, and acne. (6)

To report SUSPECTED ADVERSE REACTIONS, contact Galderma Laboratories, L.P. at 1-866-735-4137 or FDA at 1-800-FDA-1088 or www.fda.gov/medwatch.

8 USE IN SPECIFIC POPULATIONS

TRI-LUMA Cream contains the teratogen, tretinoin, which may cause embryofetal death, altered fetal growth, congenital malformations, and potential neurologic deficits. TRI-LUMA Cream should be used during pregnancy only if the potential benefit justifies the potential risk to the fetus. (8.1)

FULL PRESCRIBING INFORMATION

1 INDICATIONS AND USAGE

1.1 Indication

TRI-LUMA Cream is a combination of fluocinolone acetonide (a corticosteroid), hydroquinone (a melanin synthesis inhibitor), and tretinoin (a retinoid) that is indicated for the short-term treatment of moderate to severe melasma of the face, in the presence of measures for sun avoidance, including the use of sunscreens.

1.2 Limitations of Use

TRI-LUMA Cream is NOT indicated for the maintenance treatment of melasma. After achieving control with TRI-LUMA Cream, some patients may be managed with other treatments instead of triple therapy with TRI-LUMA Cream. Melasma usually recurs upon discontinuation of TRI-LUMA Cream.

The safety and efficacy of TRI-LUMA Cream in patients of Fitzpatrick Skin Types V and VI have not been studied. Excessive bleaching resulting in undesirable cosmetic effect in patients with darker skin cannot be excluded.

The safety and efficacy of TRI-LUMA Cream in the treatment of hyperpigmentation conditions other than melasma of the face have not been studied.

Because pregnant and lactating women were excluded from, and women of childbearing potential had to use birth control measures in the clinical trials, the safety and efficacy of TRI-LUMA Cream in pregnant women and nursing mothers have not been established [ see Use in Specific Populations (8.1, 8.3)].

2 DOSAGE AND ADMINISTRATION

Apply a thin film of TRI-LUMA Cream to the effected area once daily, at least 30 minutes before bedtime.

Gently wash the face and neck with a mild cleanser. Rinse and pat the skin dry. Apply TRI-LUMA Cream to the hyperpigmented areas of melasma including about 1/2 inch of normal appearing skin surrounding each lesion. Rub lightly and uniformly into the skin.

Therapy should be discontinued when control is achieved.

During the day, use a sunscreen of SPF 30, and wear protective clothing. Avoid sunlight exposure. Patients may use moisturizers and/or cosmetics during the day.

TRI-LUMA Cream is for topical use only. It is not for oral, ophthalmic, or intravaginal use.

3 DOSAGE FORMS AND STRENGTHS

Cream, 0.01%/4%/0.05%.

Each gram of TRI-LUMA Cream contains 0.1 mg of fluocinolone acetonide, 40 mg of hydroquinone, and 0.5 mg of tretinoin in a light yellow, hydrophilic cream base.

4 CONTRAINDICATIONS

TRI-LUMA Cream is contraindicated in individuals with a history of hypersensitivity to this product or any of its components.

5 WARNINGS AND PRECAUTIONS

5.1 Hypersensitivity

TRI-LUMA Cream contains sodium metabisulfite, a sulfite that may cause allergic-type reactions including anaphylactic symptoms and life-threatening asthmatic episodes in susceptible individuals. If anaphylaxis, asthma or other clinically significant hypersensitivity reactions occur, institute appropriate therapy and discontinue TRI-LUMA. Allergic contact dermatitis may also occur [ see Warnings and Precautions 5.4].

5.2 Exogenous Ochronosis

TRI-LUMA Cream contains hydroquinone, which may produce exogenous ochronosis, a gradual blue-black darkening of the skin, the occurrence of which should prompt discontinuation of therapy. The majority of patients developing this condition are Black, but it may also occur in Caucasians and Hispanics.

5.3 Effects on Endocrine System

TRI-LUMA Cream contains the corticosteroid fluocinolone acetonide. Systemic absorption of topical corticosteroids can produce reversible hypothalamic-pituitary-adrenal (HPA) axis suppression with the potential for glucocorticosteroid insufficiency after withdrawal of treatment. Manifestations of Cushing’s syndrome, hyperglycemia, and glucosuria can also be produced by systemic absorption of topical corticosteroid while on treatment. If HPA axis suppression is noted, the use of TRI-LUMA Cream should be discontinued. Recovery of HPA axis function generally occurs upon discontinuation of topical corticosteroids.

The ACTH or cosyntropin stimulation test may be helpful in evaluating patients for HPA axis suppression.

5.4 Cutaneous Reactions

Cutaneous hypersensitivity to the active ingredients of TRI-LUMA Cream has been reported in the literature. In a patch test study to determine sensitization potential in 221 healthy volunteers, three volunteers developed sensitivity reactions to TRI-LUMA Cream or its components.

TRI-LUMA Cream contains hydroquinone and tretinoin that may cause mild to moderate irritation. Local irritation, such as skin reddening, peeling, mild burning sensation, dryness, and pruritus may be expected at the site of application. Transient skin reddening or mild burning sensation does not preclude treatment. If a reaction suggests hypersensitivity or chemical irritation, the use of the medication should be discontinued.

Patients should avoid medicated or abrasive soaps and cleansers, soaps and cosmetics with drying effects, products with high concentrations of alcohol and astringents, and other irritants or keratolytic drugs while on TRI-LUMA Cream treatment. Patients are cautioned on concomitant use of medications that are known to be photosensitizing.

6 ADVERSE REACTIONS

Because clinical trials are conducted under widely varying conditions, adverse reaction rates observed in the clinical trials of a drug cannot be directly compared to rates in the clinical trials of another drug and may not reflect the rates observed in clinical practice.

In the controlled clinical trials, adverse events were monitored in the 161 subjects who used TRI-LUMA Cream once daily during an 8-week treatment period. There were 102 (63%) subjects who experienced at least one treatment-related adverse event during these trials. The most frequently reported events were erythema, desquamation, burning, dryness, and pruritus at the site of application. The majority of these events were mild to moderate in severity. Adverse events reported by at least 1% of patients and judged by the investigators to be reasonably related to treatment with TRI-LUMA Cream from the controlled clinical trials are summarized (in decreasing order of frequency) as follows:

Table 1. Incidence and Frequency of Treatment-related Adverse Events with TRI-LUMA Cream in at least 1% or more of Subjects (N=161)
Adverse Event | n (%)
Erythema | 66 (41%)
Desquamation | 61 (38%)
Burning | 29 (18%)
Dryness | 23 (14%)
Pruritus | 18 (11%)
Acne | 8 (5%)
Paresthesia | 5 (3%)
Telangiectasia | 5 (3%)
Hyperesthesia | 3 (2%)
Pigmentary changes | 3 (2%)
Irritation | 3 (2%)
Papules | 2 (1%)
Acne-like rash | 1 (1%)
Rosacea | 1 (1%)
Dry Mouth | 1 (1%)
Rash | 1 (1%)
Vesicles | 1 (1%)

In an open-label trial, subjects who had cumulative treatment of melasma with TRI-LUMA Cream for 6 months showed a similar pattern of adverse events as in the 8-week studies.

The following local adverse reactions have been reported with topical corticosteroids. They may occur more frequently with the use of occlusive dressings, especially with higher potency corticosteroids. These reactions are listed in an approximate decreasing order of occurrence: burning, itching, irritation, dryness, folliculitis, acneiform eruptions, hypopigmentation, perioral dermatitis, allergic contact dermatitis, secondary infection, skin atrophy, striae, and miliaria.

8 USE IN SPECIFIC POPULATIONS

8.1 Pregnancy

Teratogenic Effects: Pregnancy Category C

There are no adequate and well-controlled studies in pregnant women. TRI-LUMA Cream should be used during pregnancy only if the potential benefit justifies the potential risk to the fetus. TRI-LUMA Cream contains the teratogen, tretinoin, which may cause embryo-fetal death, altered fetal growth, congenital malformations, and potential neurologic deficits.

In clinical trials involving TRI-LUMA Cream in the treatment of facial melasma, women of child-bearing potential initiated treatment only after having had a negative pregnancy test and used effective birth control measures during therapy. However, 13 women became pregnant during treatment with TRI-LUMA Cream. Most of the pregnancy outcomes are unknown. Three women gave birth to apparently healthy babies. One pregnancy was terminated prematurely, and another ended in miscarriage.

In general, use of drugs should be reduced to a minimum in pregnancy. If a patient has been inadvertently exposed to TRI-LUMA Cream in pregnancy, she should be counseled on the risk of teratogenesis due to this exposure. The risk of teratogenesis due to topical exposure to TRI-LUMA Cream may be considered low. However, exposure during the period of organogenesis in the first trimester is theoretically more likely to produce adverse outcome than in later pregnancy.

Tretinoin is considered to be highly teratogenic upon systemic administration. Animal reproductive studies are not available with topical hydroquinone. Corticosteroids have been shown to be teratogenic in laboratory animals when administered systemically at relatively low dosage levels. Some corticosteroids have been shown to be teratogenic after dermal application in laboratory animals.

• In a dermal application study using TRI-LUMA Cream in pregnant rabbits, there was an increase in the number of in uterodeaths and a decrease in fetal weights in litters from dams treated topically with the drug product.

• In a dermal application study in pregnant rats treated with TRI-LUMA Cream during organogenesis there was evidence of teratogenicity of the type expected with tretinoin. These morphological alterations included cleft palate, protruding tongue, open eyes, umbilical hernia, and retinal folding or dysplasia.

• In a dermal application study on the gestational and postnatal effects of a 10-fold dilution of TRI-LUMA Cream in rats, an increase in the number of stillborn pups, lower pup body weights, and delay in preputial separation were observed. An increase in overall activity was seen in some treated litters at postnatal day 22 and in all treated litters at five weeks, a pattern consistent with effects previously noted in animals exposed in uterowith retinoic acids. No adequate study of the late gestational and postnatal effects of the full-strength TRI-LUMA Cream has been performed.

• It is difficult to interpret these animal studies on teratogenicity with TRI-LUMA Cream, because the availability of the dermal applications in these studies could not be assured, and comparison with clinical dosing is not possible.

8.3 Nursing Mothers

Corticosteroids, when systemically administered, appear in human milk. It is not known whether topical application of TRI-LUMA Cream could result in sufficient systemic absorption to produce detectable quantities of fluocinolone acetonide, hydroquinone, or tretinoin in human milk. Because many drugs are secreted in human milk, caution should be exercised when TRI-LUMA Cream is administered to a nursing woman. Care should be taken to avoid contact between the infant being nursed and TRI-LUMA Cream.

8.4 Pediatric use

Safety and effectiveness of TRI-LUMA Cream in pediatric patients have not been established.

8.5 Geriatric Use

Clinical studies of TRI-LUMA Cream did not include sufficient number of subjects aged 65 and over to determine whether they respond differently from younger subjects. Other reported clinical experience has not identified differences in responses between the elderly and younger patients. In general, dose selection for an elderly patient should be cautious, usually starting at the low end of the dosing range, reflecting the greater frequency of decreased hepatic, renal or cardiac function, and of concomitant disease or other drug therapy.

11 DESCRIPTION

TRI-LUMA (fluocinolone acetonide, hydroquinone, and tretinoin) Cream, 0.01%/4%/0.05% contains fluocinolone acetonide, USP, hydroquinone, USP, and tretinoin, USP, in a light yellow, hydrophilic cream base for topical application.

Fluocinolone acetonide is a synthetic fluorinated corticosteroid. It is a white crystalline powder that is odorless and stable in light.

The chemical name for fluocinolone acetonide is: (6α,11β,16α)-6,9-difluoro-11,21-dihydroxy-16,17-[(1-methylethylidene)bis(oxy)]-pregna-1,-4-diene-3,20-dione.

The molecular formula is C24H30F2O6and molecular weight is 452.50.

Fluocinolone acetonide has the following structural formula:

Hydroquinone is a melanin synthesis inhibitor. It is prepared from the reduction of p-benzoquinone with sodium bisulfite. It occurs as fine white needles that darken on exposure to air.

The chemical name for hydroquinone is: 1,4-benzenediol.

The molecular formula is C6H6O2and molecular weight is 110.11.

Hydroquinone has the following structural formula:

Tretinoin, a retinoid, is all- trans-retinoic acid formed from the oxidation of the aldehyde group of retinene to a carboxyl group. It occurs as yellow to light-orange crystals or crystalline powder with a characteristic odor of ensilage. It is highly reactive to light and moisture.

The chemical name for tretinoin is: (all-E)-3,7-dimethyl-9-(2,6,6-trimethyl-1-cyclohexen-1-yl)-2,4,6,8-nonatetraenoic acid.

The molecular formula is C20H28O2and molecular weight is 300.44.

Tretinoin has the following structural formula:

Each gram of TRI-LUMA Cream contains Active:fluocinolone acetonide 0.01% (0.1 mg), hydroquinone 4% (40 mg), and tretinoin 0.05% (0.5 mg). Inactive:butylated hydroxytoluene, cetyl alcohol, citric acid anhydrous, glycerin, glyceryl stearate, magnesium aluminum silicate, methyl gluceth-10, methylparaben, PEG-100 stearate, propylparaben, purified water, sodium metabisulfite, stearic acid, and stearyl alcohol.

12 CLINICAL PHARMACOLOGY

12.1 Mechanism of Action

The mechanism of action of the active ingredients in TRI-LUMA Cream in the treatment of melasma is unknown.

12.3 Pharmacokinetics

Percutaneous absorption of unchanged tretinoin, hydroquinone and fluocinolone acetonide into the systemic circulation of two groups of healthy volunteers (Total N=59) was found to be minimal following 8 weeks of daily application of 1g (Group I, n=45) or 6g (Group II, n=14) of TRI-LUMA Cream.

For tretinoin quantifiable plasma concentrations were obtained in 57.78% (26 out of 45) of Group I and 57.14% (8 out of 14) of Group II subjects. The exposure to tretinoin as reflected by the Cmaxvalues ranged from 2.01 to 5.34 ng/mL (Group I) and 2.0 to 4.99 ng/mL (Group II). Thus, daily application of TRI-LUMA Cream resulted in a minimal increase of normal endogenous levels of tretinoin. The circulating tretinoin levels represent only a portion of total tretinoin-associated retinoids, which would include metabolites of tretinoin and that sequestered into peripheral tissues.

For hydroquinone, quantifiable plasma concentrations were obtained in 18% (8 out of 44) Group I subjects. The exposure to hydroquinone, as reflected by the Cmaxvalues, ranged from 25.55 to 86.52 ng/mL. All Group II subjects (6g dose) had post-dose plasma hydroquinone concentrations below the quantitation limit. For fluocinolone acetonide, Groups I and II subjects had all post-dose plasma concentrations below quantitation limit.

13 NONCLINICAL TOXICOLOGY

13.1 Carcinogenesis, Mutagenesis, Impairment of Fertility

When fluocinolone acetonide, hydroquinone, and tretinoin in fixed combinations equivalent to 10%, 50%, 100%, and 150% of the concentrations in the clinical formulation of TRI-LUMA Cream were applied topically to male and female CD-1 mice for up to 24 months at dosages approximating up to 50, 19,000, and 250 µg/kg/day, respectively (corresponding to dosages of 150, 57,000, and 750 μg/m^2/day, respectively), no statistically significant changes in tumor incidence were observed.

When fluocinolone acetonide, hydroquinone, and tretinoin in fixed combinations equivalent to 10%, 25%, 50%, and 100% of the concentrations in the clinical formulation of TRI-LUMA Cream were applied topically to male and female SD rats for up to 24 months at dosages approximating up to 10, 4000, and 50 µg/kg/day, respectively (corresponding to dosages of 60, 24,000, and 300 μg/m^2/day, respectively), statistically significant increases in the incidences of islet cell adenomas and combined islet cell adenomas and carcinomas of the pancreas in both males and females were observed. The clinical relevance of these findings is unknown.

Studies of hydroquinone in animals have demonstrated some evidence of carcinogenicity. The carcinogenic potential of hydroquinone in humans is unknown.

Studies in hairless albino mice suggest that concurrent exposure to tretinoin may enhance the tumorigenic potential of carcinogenic doses of UVB and UVA light from a solar simulator. This effect has been confirmed in a later study in pigmented mice, and dark pigmentation did not overcome the enhancement of photocarcinogenesis by 0.05% tretinoin. Although the significance of these studies to humans is not clear, patients should minimize exposure to sunlight or artificial ultraviolet irradiation sources.

Mutagenicity studies were not conducted with this combination of active ingredients. Published studies have demonstrated that hydroquinone is a mutagen and a clastogen. Treatment with hydroquinone has resulted in positive findings for genetic toxicity in the Ames assay in bacterial strains sensitive to oxidizing mutagens, in in vitrostudies in mammalian cells, and in the in vivomouse micronucleus assay. Tretinoin has been shown to be negative for mutagenesis in the Ames assay. Additional information regarding the genetic toxicity potential of tretinoin and of fluocinolone acetonide is not available.

A dermal reproductive fertility study was conducted in SD rats using a 10-fold dilution of the clinical formulation. No effect was seen on the traditional parameters used to assess fertility, although prolongation of estrus was observed in some females, and there was a trend towards an increase in pre-and post-implantation loss that was not statistically significant. No adequate study of fertility and early embryonic toxicity of the full-strength drug product has been performed. In a six-month study in minipigs, small testes and severe hypospermia were found when males were treated topically with the full strength drug product.

14 CLINICAL STUDIES

Two adequate and well-controlled efficacy and safety trials were conducted in 641 subjects between the ages of 21 to 75 years, having Fitzpatrick Skin types I-IV and moderate to severe melasma of the face. TRI-LUMA Cream was compared with 3 possible combinations of 2 of the 3 active ingredients [(1) hydroquinone 4% (HQ) + tretinoin 0.05% (RA); (2) fluocinolone acetonide 0.01% (FA) + tretinoin 0.05% (RA); (3) fluocinolone acetonide 0.01% (FA) + hydroquinone 4% (HQ)], contained in the same vehicle as TRI-LUMA Cream. Subjects were instructed to apply their study medication each night, after washing their face with a mild soapless cleanser, for 8 weeks. Instructions were given to apply a thin layer of study medication to the hyperpigmented lesion, making sure to cover the entire lesion including the outside borders extending to the normal pigmented skin. Subjects were provided a mild moisturizer for use as needed. A sunscreen with SPF 30 was also provided with instructions for daily use. Protective clothing and avoidance of sunlight exposure to the face was recommended.

Subjects were evaluated for melasma severity at Baseline and at Weeks 1, 2, 4, and 8 of treatment. Primary efficacy was based on the proportion of subjects who had an investigators’ assessment of treatment success, defined as the clearing of melasma at the end of the eight-week treatment period. The majority of subjects enrolled in the two trials were white (approximately 66%) and female (approximately 98%). TRI-LUMA Cream was demonstrated to be significantly more effective than any of the other combinations of the active ingredients.

PRIMARY EFFICACY ANALYSIS:

Table 2. Investigators' Assessment of Treatment Success [Treatment success was defined as melasma severity score of zero (melasma lesions cleared of hyperpigmentation)] At the End of 8 Weeks of Treatment
 |  | TRI-LUMA | HQ+RA | FA+RA | FA+HQ
Trial 1 | Subjects, n | 85 | 83 | 85 | 85
Trial 1 | Successes, n | 32 | 12 | 0 | 3
Trial 1 | Proportion of Successes | 38% | 15% | 0 | 4%
Trial 1 | p-value |  | ‹ 0.001 | ‹ 0.001 | ‹ 0.001
Trial 2 | Subjects, n | 76 | 75 | 76 | 76
Trial 2 | Successes, n | 10 | 3 | 3 | 1
Trial 2 | Proportion of Successes | 13% | 4% | 4% | 1%
Trial 2 | p-value |  | 0.045 | 0.042 | 0.005

p-value is from Cochran-Mantel-Haenszel chi-square statistics controlling for pooled investigator and comparing TRI-LUMA Cream to the other treatment groups.

In the Investigators’ assessment of melasma severity at Day 56 of treatment, the following table shows the clinical improvement profile for all subjects treated with TRI-LUMA Cream based on severity of their melasma at the start of treatment.

Table 3. Investigators' Assessment of Change in Melasma Severity from Baseline to Day 56 of Treatment (combined results from trials 1 and 2)
 |  |  | Number (%) of Subjects at Day 56 [Assessment based on subjects with severity scores at Day 56. Percentages are bases on the total number in the treatment group population.]
 | Baseline |  | Cleared [Does not include subjects who cleared before Day 56 or were missing from the Day 56 Assessment] | Mild | Moderate | Severe | Missing
 | Severity Rating | n | n (%) | n (%) | n (%) | n (%) | n (%)
TRI-LUMA Cream N=161 | Moderate | 124 | 36 (29) | 63 (51) | 18 (15) | 0 (0) | 7 (6)
TRI-LUMA Cream N=161 | Severe | 37 | 6 (16) | 19 (51) | 9 (24) | 2 (5) | 1 (3)

Assessment Scale: Cleared (melasma lesions approximately equivalent to surrounding normal skin or with minimal residual hyperpigmentation); Mild (slightly darker than the surrounding normal skin); Moderate (moderately darker than the surrounding normal skin); Severe (markedly darker than the surrounding normal skin).

Subjects experienced improvement of their melasma with the use of TRI-LUMA Cream as early as 4 weeks. However, among 7 subjects who had clearing at the end of 4 weeks of treatment with TRI-LUMA Cream, 4 of them did not maintain the remission after an additional 4 weeks of treatment.

After 8 weeks of treatment with the trial drug, subjects entered into an open-label extension period in which TRI-LUMA Cream was given on an as-needed basis for the treatment of melasma. The remission periods appeared to shorten between progressive courses of treatment. Additionally, few subjects maintained complete clearing of melasma (approximately 1 to 2%).

16 HOW SUPPLIED/STORAGE AND HANDLING

TRI-LUMA Cream is light yellow in color, and supplied in 30 g aluminum tubes, NDC0299-5950-30.

Storage: Keep tightly closed. Store in a refrigerator, 2° - 8°C (36° - 46°F). Protect from freezing.

17 PATIENT COUNSELING INFORMATION

See FDA-approved patient labeling (Patient Information)

Inform patients of the following:

- Advise patients to change to non-hormonal forms of birth control, if hormonal methods are used.
- Use TRI-LUMA Cream as directed by the health care provider and do not use TRI-LUMA Cream for any disorder other than that for which it is prescribed.
- Avoid exposure to sunlight, sunlamp, or ultraviolet light. Patients who are consistently exposed to sunlight or skin irritants either through their work environment or habits should exercise particular caution. Use sunscreen and protective covering (such as the use of a hat) over the treated areas. Sunscreen use is an essential aspect of melasma therapy, as even minimal sunlight sustains melanocytic activity.
- Weather extremes, such as heat or cold, may be irritating to patients treated with TRI-LUMA Cream. Because of the drying effect of this medication, a moisturizer may be applied to the face in the morning after washing.
- Keep TRI-LUMA Cream away from the eyes, nose, angles of the mouth, or open wounds because these areas are more sensitive to the irritant effect. If local irritation persists or becomes severe, discontinue application of the medication and consult your health care provider. Seek medical attention if you experience allergic contact dermatitis, blistering, crusting, and severe burning or swelling of the skin and irritation of the mucous membranes of the eyes, nose, and mouth.
- If the medication is applied excessively, marked redness, peeling, or discomfort may occur.
- Wash your hands after each application.

Marketed by:

GALDERMA LABORATORIES, L.P.

Dallas, TX 75201 USA

Manufactured by:

Hill Dermaceuticals, Inc.

Sanford, FL 32773 USA

P51400-2

PATIENT INFORMATION

TRI-LUMA®(try-LOOM-ah)

(fluocinolone acetonide 0.01%, hydroquinone 4%, and tretinoin 0.05%)

Cream

Important information: TRI-LUMA Cream is for use on skin only. Do not use TRI-LUMA Cream in your mouth, eyes, or vagina.

What is the most important information I should know about TRI-LUMA Cream?

TRI-LUMA Cream may cause birth defects or death of the baby if used during pregnancy.The risk of birth defects or death of the baby may be greater if TRI-LUMA Cream is used during the first trimester of pregnancy. Tell your doctor if you are pregnant or plan to become pregnant.

If you become pregnant while using TRI-LUMA Cream, tell your doctor right away.

What is TRI-LUMA Cream?

TRI-LUMA Cream is a prescription medicine used for the short-term treatment of moderate to severe melasma of the face, in combination with sun avoidance and the use of sunscreens.

TRI-LUMA Cream is not for continuous treatment of melasma.

It is not known if TRI-LUMA Cream is safe and effective in children.

It is not known if TRI-LUMA Cream is safe and effective in people with dark brown to black skin color.

It is not known if TRI-LUMA Cream is safe and effective in the treatment of dark spots (hyperpigmentation) of the skin caused by conditions other than melasma of the face.

It is not known if TRI-LUMA Cream is safe and effective in females who are pregnant or who are breastfeeding. See "What is the most important information I should know about TRI-LUMA Cream?and What should I tell my doctor before using TRI-LUMA Cream?"

Who should not use TRI-LUMA Cream?

Do not use TRI-LUMA Cream if you are allergic to it or any of the ingredients in TRI-LUMA Cream. See the end of this leaflet for a complete list of ingredients in TRI-LUMA Cream.

What should I tell my doctor before using TRI-LUMA Cream?

Before you use TRI-LUMA Cream, tell your doctor if you:

- are allergic to sulfites
- have any other medical conditions
- are pregnant or plan to become pregnant. See "What is the most important information I should know about TRI-LUMA Cream?"
- are breastfeeding or plan to breastfeed. It is not known if TRI-LUMA Cream passes into your breast milk. You should avoid skin-to-skin contact between areas treated with TRI-LUMA Cream and your baby.

Tell your doctor about all the medicines you take,including prescription and over-the-counter medicines, vitamins, herbal supplements and skin products that you use.

How should I use TRI-LUMA Cream?

- Use TRI-LUMA Cream exactly as your doctor tells you to use it.
- Before you apply TRI-LUMA Cream, gently wash your face with a mild cleanser. Rinse your face and pat your skin dry.
- Apply TRI-LUMA Cream 1 time a day, at least 30 minutes before bedtime.
- Apply a thin layer of TRI-LUMA Cream to the affected skin areas. Include about 1/2 inch of normal skin surrounding the affected area.
- Gently rub TRI-LUMA Cream evenly into your skin.
- Do not get TRI-LUMA Cream near the corners of your mouth, your nose, your eyes, or open wounds.
- Do not bandage or cover the treated skin after applying TRI-LUMA Cream.
- You may use moisturizers and cosmetics during the day.
- Wash your hands after applying TRI-LUMA Cream.

What should I avoid while using TRI-LUMA Cream?

- You should avoid sunlight, sunlamps, tanning beds, and ultraviolet light during treatment with TRI-LUMA Cream.
  - Use a sunscreen with SPF (sun protection factor) of 30 or more. If you have to be in the sunlight, wear a wide-brimmed hat or other protective clothing to cover the treated areas.
  - Melasma can get worse with even a small amount of sunlight. You should continue to avoid sunlight, use sunscreen, and wear protective clothing after treatment with TRI-LUMA Cream.

- Females should avoid the use of hormonal forms of birth control. Hormonal birth control methods can cause your melasma to become worse. Talk to your doctor about other birth control options.
- Heat and cold weather may irritate skin treated with TRI-LUMA. Talk with your doctor about ways to manage skin irritation.

What are the possible side effects of TRI-LUMA Cream?

TRI-LUMA Cream may cause serious side effects, including:

- allergic reactions. TRI-LUMA Cream may cause allergic reactions that can be life threatening. Stop using TRI-LUMA Cream and call your doctor to get medical help right away if you get any of the following symptoms:
  - swelling of your face, eyes, lips, tongue, or throat
  - trouble breathing
  - severe itching
  - skin rash or hives

- change in skin color. One of the medicines in TRI-LUMA Cream can cause a blue-black darkening of your skin. Stop using TRI-LUMA Cream and tell your doctor if you develop a blue-black darkening of your skin.

• TRI-LUMA Cream can pass through your skin.Too much TRI-LUMA Cream passing through your skin can cause your adrenal glands to stop working. Your doctor may do blood tests to check for adrenal gland problems.

- skin irritation. Stop using TRI-LUMA Cream and call your doctor if you have:
  - blistering or crusting of your skin
  - severe burning
  - swelling of your skin
  - irritation of your eyes, nose, or mouth

The most common side effects of TRI-LUMA Cream include:

- redness
- peeling
- burning
- dryness
- itching
- acne

Tell your doctor if you have any side effect that bothers you or that does not go away.

These are not all the possible side effects of TRI-LUMA Cream. For more information, ask your doctor or pharmacist.

Call your doctor for medical advice about side effects. You may report side effects to FDA at 1-800-FDA-1088.

You may also report side effects to Galderma Laboratories, L.P. at 1-866-735-4137.

How should I store TRI-LUMA Cream?

- Store TRI-LUMA Cream in a refrigerator, between 36°F to 46°F (2°C to 8 °C).
- Keep TRI-LUMA Cream tube tightly closed.
- Do not freeze TRI-LUMA Cream.

General information about the safe and effective use of TRI-LUMA Cream

Medicines are sometimes prescribed for purposes other than those listed in a Patient Information leaflet. Do not use TRI-LUMA Cream for a condition for which it was not prescribed. Do not give TRI-LUMA Cream to other people, even if they have the same symptoms you have. It may harm them.

If you would like more information, talk with your doctor. You can ask your pharmacist or doctor for information about TRI-LUMA Cream that is written for health professionals.

What are the ingredients in TRI-LUMA Cream?

Active ingredients:fluocinolone acetonide, hydroquinone, and tretinoin

Inactive ingredients:butylated hydroxytoluene, cetyl alcohol, citric acid anhydrous, glycerin, glyceryl stearate, magnesium aluminum silicate, methyl gluceth-10, methylparaben, PEG-100 stearate, propylparaben, purified water, sodium metabisulfite, stearic acid, and stearyl alcohol

This Patient Information has been approved by the U.S. Food and Drug Administration.

Marketed by:

GALDERMA LABORATORIES, L.P.

Dallas, TX 75201 USA

Manufactured by:

Hill Dermaceuticals, Inc.

Sanford, FL 32773 USA
P51400-2

30g Carton Label

Tri-Luma®(fluocinolone acetonide, hydroquinone, tretinoin) cream, 0.01%/4%/0.05%
NDC 0299-5950-30
Rx Only
MUST BE REFRIGERATED
NET WT. 30 g
GALDERMA

For Topical Use Only. Not for Ophthalmic Use.
Usual dosage:Apply a thin film affected areas once daily at night. See package insert for complete prescribing information.
Each gram contains: Active: fluocinolone acetonide 0.01% (0.1 mg), hydroquinone 4% (40 mg), and tretinoin 0.05% (.5 mg). Inactive:butylated hydroxytoluene, cetyl alcohol, citric acid anhydrous, glycerin, glyceryl stearate, magnesium aluminum silicate, methyl gluceth-10, methylparaben, PEG-100 stearate, propylparaben, purified water, sodium metabisulfite, stearic acid, and stearyl alcohol.
Storage: Store in a refrigerator, 2° to 8° C (36° to 46° F). Protect from freezing.
See carton closure for lot number and expiration date.
www.triluma.com

MUST BE REFRIGERATED
Marketed by:
GALDERMA LABORATORIES, L.P.
Dallas, TX 75201 USA

All trademarks are the property of their respective owners.
P51399-6